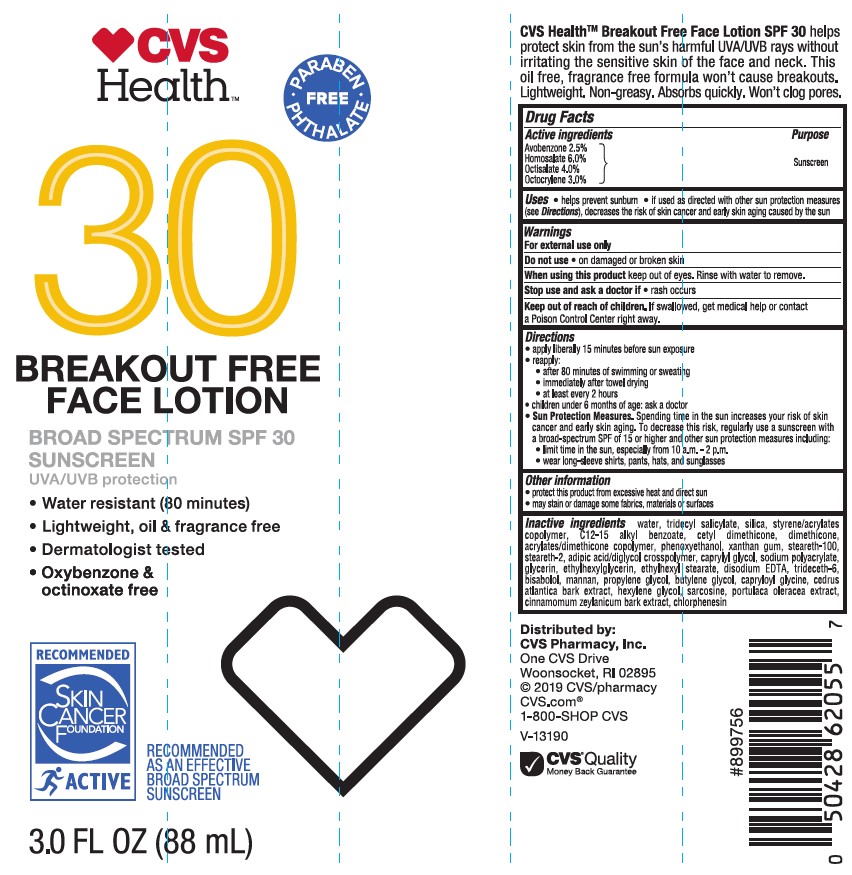 DRUG LABEL: CVS Health SPF 30 Breakout Free Face
NDC: 51316-033 | Form: LOTION
Manufacturer: CVS PHARMACY
Category: otc | Type: HUMAN OTC DRUG LABEL
Date: 20241017

ACTIVE INGREDIENTS: HOMOSALATE 60 mg/1 mL; OCTISALATE 40 mg/1 mL; OCTOCRYLENE 30 mg/1 mL; AVOBENZONE 25 mg/1 mL
INACTIVE INGREDIENTS: TRIDECYL SALICYLATE; WATER; STYRENE/ACRYLAMIDE COPOLYMER (MW 500000); ALKYL (C12-15) BENZOATE; CINNAMON BARK OIL; PROPYLENE GLYCOL; BUTYLENE GLYCOL; PURSLANE; CHLORPHENESIN; ADIPIC ACID/DIGLYCOL CROSSPOLYMER (20000 MPA.S); GLYCERIN; ACRYLIC ACID; BUTYLATED HYDROXYTOLUENE; EDETATE DISODIUM ANHYDROUS; TRIDECETH-6; LEVOMENOL; KONJAC MANNAN; CAPRYLOYL GLYCINE; STEARETH-100; ETHYLHEXYL STEARATE; SILICON DIOXIDE; CEDRUS ATLANTICA BARK; STEARETH-2; CAPRYLYL GLYCOL; ETHYLHEXYLGLYCERIN; HEXYLENE GLYCOL; SARCOSINE; DIMETHICONE; PHENOXYETHANOL; XANTHAN GUM; CETYL DIMETHICONE 45; SODIUM POLYACRYLATE (8000 MW)

CVS Health SPF 30 Breakout Free Face Lotion

Active ingredients

Avobenzone 2.5%, Homosalate 6.0%, Octisalate 4.0%, Octocrylene 3.0%

Purpose

Sunscreen

Uses

- helps prevent sunburn
- if used as directed with other sun protection measures (see Directions), decreases the risk of skin cancer and early aging caused by the sun

Warnings

For external use only

Do not use on

• on damaged or broken skin

When using this product

• keep out of eyes. Rinse with water to remove.

Stop use and ask a doctor if

• rash occurs

Keep out of reach of children.

If swallowed, get medical help or contact a Poison Control Center right away.

Directions

- apply liberally 15 minutes before sun exposure
- Reapply:
- after 80 minutes of swimming or sweating
- immediately after towel drying
- at least every 2 hours
- children under 6 months of age: Ask a doctor
- Sun Protection Measures. Spending time in the sun increases your risk of skin cancer and early skin aging. To decrease this risk, regularly use a sunscreen with a Broad Spectrum SPF value of 15 or higher and other sun protection measures including:
- limit time in the sun especially from 10 a.m. – 2 p.m.
- wear long-sleeved shirts, pants, hats, and sunglasses

Other Information

- protect the product in this container from excessive heat and direct sun
- may stain or damage some fabrics, materials or surfaces

Inactive ingredients

water, tridecyl salicylate, silica, styrene acrylates copolymer, C12-15 alkyl benzoate, cetyl dimethicone, dimethicone, acrylates/dimethicone copolymer, phenoxyethanol, xanthan gum, steareth-100, steareth-2, adipic acid/diglycol crosspolymer, caprylyl glycol, sodium polyacrylate, glycerin, ethylhexylglycerin, ethylhexyl stearate, disodium EDTA, trideceth-6, bisabolol, mannan, propylene glycol, butylene glycol, capryloyl glycine, cedrus atlantica bark extract, hexylene glycol, sarcosine, portulaca oleracea extract, cinnamomum zeylancium bark extract, chlorphenesin.